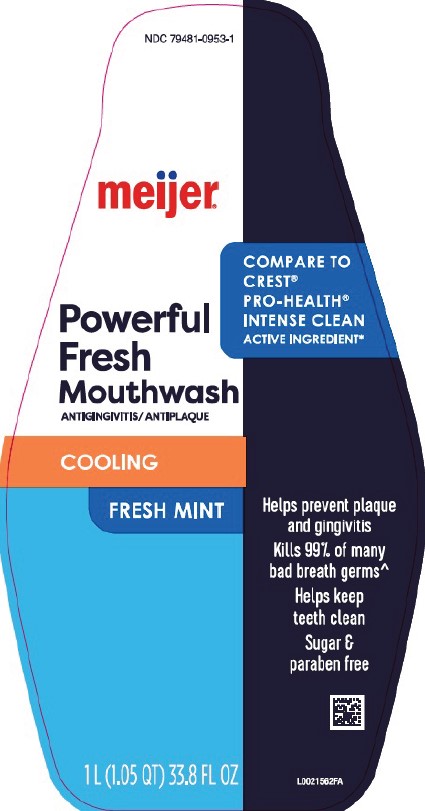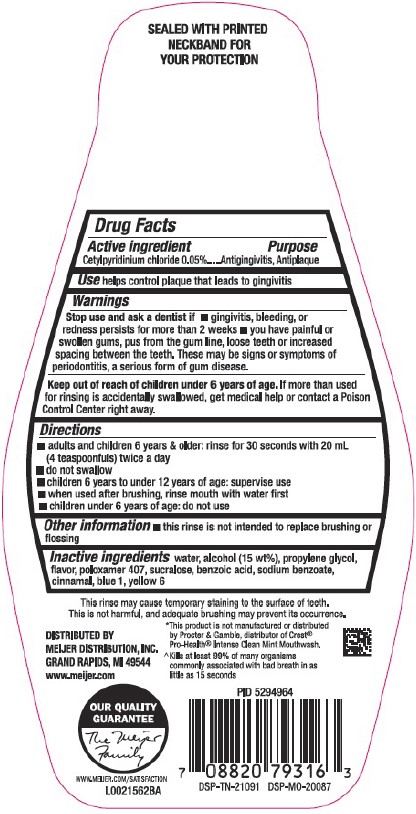 DRUG LABEL: Antigingivitis/Antiplaque
NDC: 79481-0953 | Form: MOUTHWASH
Manufacturer: Meijer, Inc.
Category: otc | Type: HUMAN OTC DRUG LABEL
Date: 20260224

ACTIVE INGREDIENTS: CETYLPYRIDINIUM CHLORIDE 0.5 mg/1 mL
INACTIVE INGREDIENTS: WATER; ALCOHOL; PROPYLENE GLYCOL; POLOXAMER 407; SUCRALOSE; BENZOIC ACID; SODIUM BENZOATE; CINNAMALDEHYDE; FD&C BLUE NO. 1; FD&C YELLOW NO. 6

Meijer D53.000/D53AA
Powerful Fresh Mint Mouthwash

Tamper Evident Statement

SEALED WITH PRINTED NECKBAND FOR YOUR PROTECTION

Active Ingredient

Cetylpyridinium Chloride 0.05%

Purpose

Antigingivitis, Antiplaque

Use

helps control plaque that leads to gingivitis

Warnings

for this product

Stop use and ask a dentist if

- gingivitis, bleeding, or redness persists for more than 2 weeks
- you have painful or swollen gums, pus from the gum line, loose teeth or increased spacing between the teeth. These may be signs or symptoms of periodontitis, a serious form of gum disease.

Keep out of reach of children under 6 years of age.

If more than used for rinsing is accidentally swallowed, get medical help or contact a Poison Control Center right away.

Directions

- adults and children 6 years & older: rinse for 30 seconds with 20 mL (4 teaspoonfuls) twice a day
- do not swallow
- children 6 years to under 12 years of age: supervise use
- when used after brushing, rinse mouth with water first
- children under 6 years of age: do not use

Other information

- this rinse is not intended to replace brushing or flossing

Inactive ingredients

water, alcohol (15 wt%), propylene glycol, flavor, poloxamer 407, sucralose, benzoic acid, sodium benzoate, cinnamal, blue 1, yellow 6

Disclaimers

This may cause temporary staining to the surface of teeth.

This is not harmful, and adequate brushing may prevent its occurrence.

*This product is not manufactured or distributed by Procter & Gamble, distributor of Crest® Pro-Health® Intense Clean Mint Mouthwash.

Claims

^Kills at least 99% of many organisims commony associated with bad breath in as little as 15 seconds.

ADVERSE REACTION

DISTRIBUTED BY

MEIJER DISTRIBUTION, INC.

GRAND RAPIDS, MI 49544

www.meijer.com

OUR QUALITY GUARANTEE

The Meijer Family

WWW.MEIJER.COM/SATISFACTION

DSP-TN-21091 DSP-MO-20087

Principal Panel Display

NDC 79481-0953-1

meijer®

COMPARE TO CREST®PRO-HEALTH®INTENSE CLEAN ACTIVE INGREDIENT*

Powerful Fresh Mouthwash

ANTIGINGIVITIS/ANTIPLAQUE

COOLING

FRESH MINT

Helps prevent plaque and gingivitis

Kills 99% of many bad breath germs^

Helps keeps teeth clean

Sugar & paraben free

1 L (1.5 QT) 33.8 FL OZ